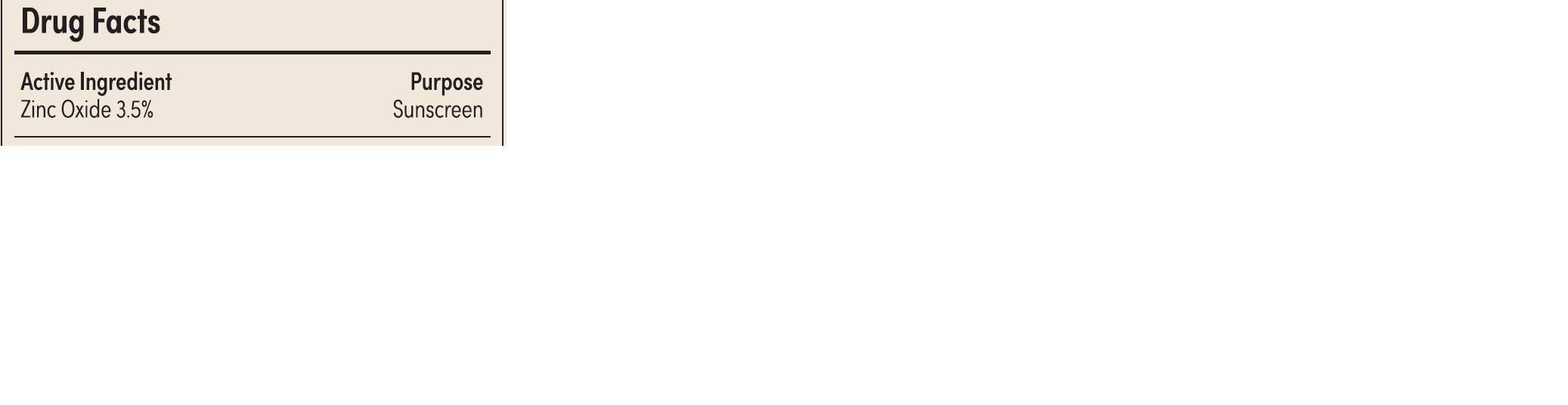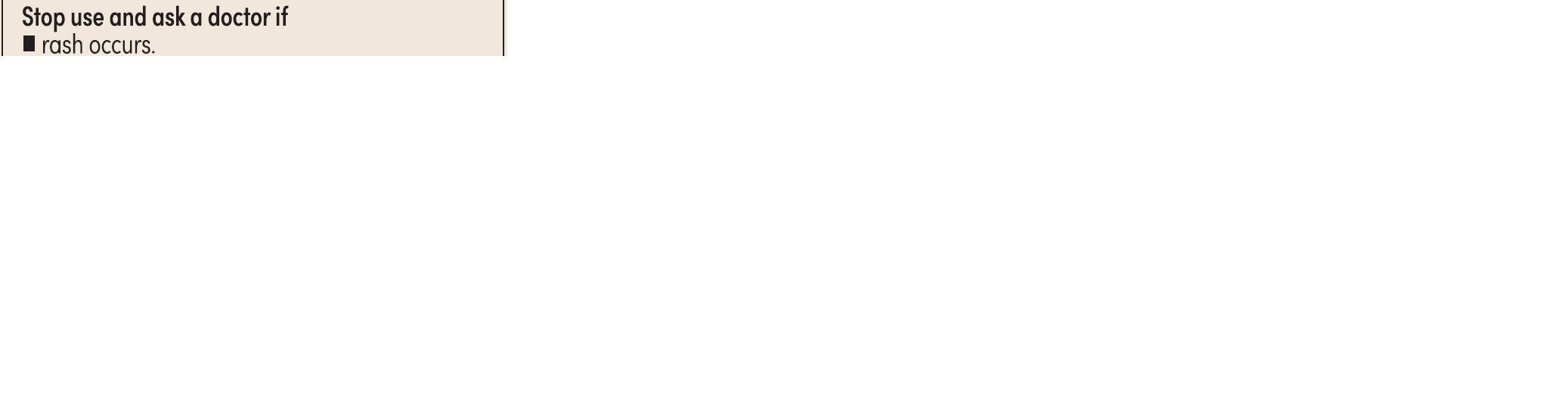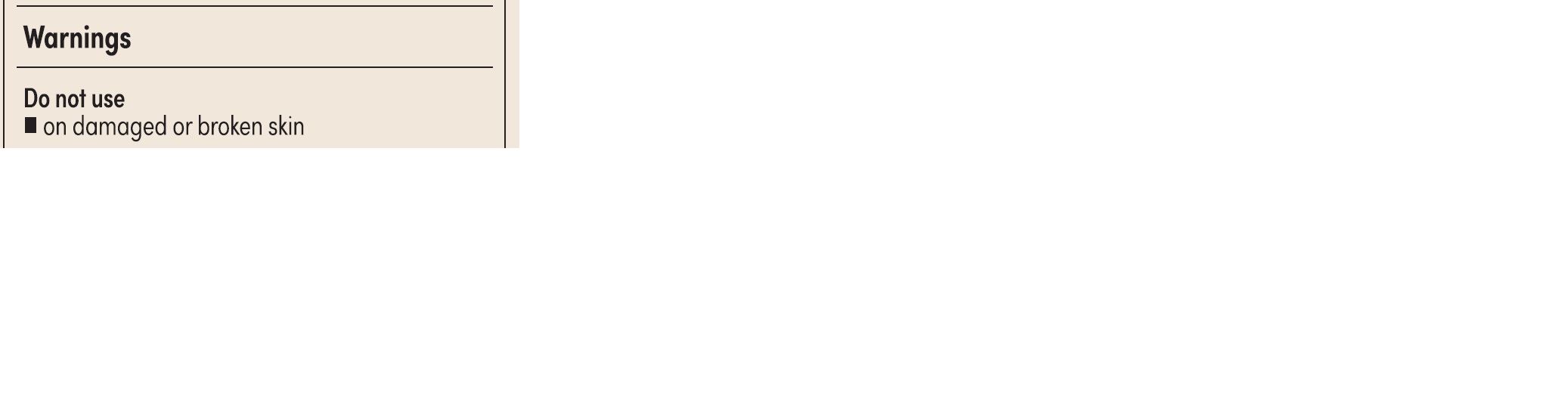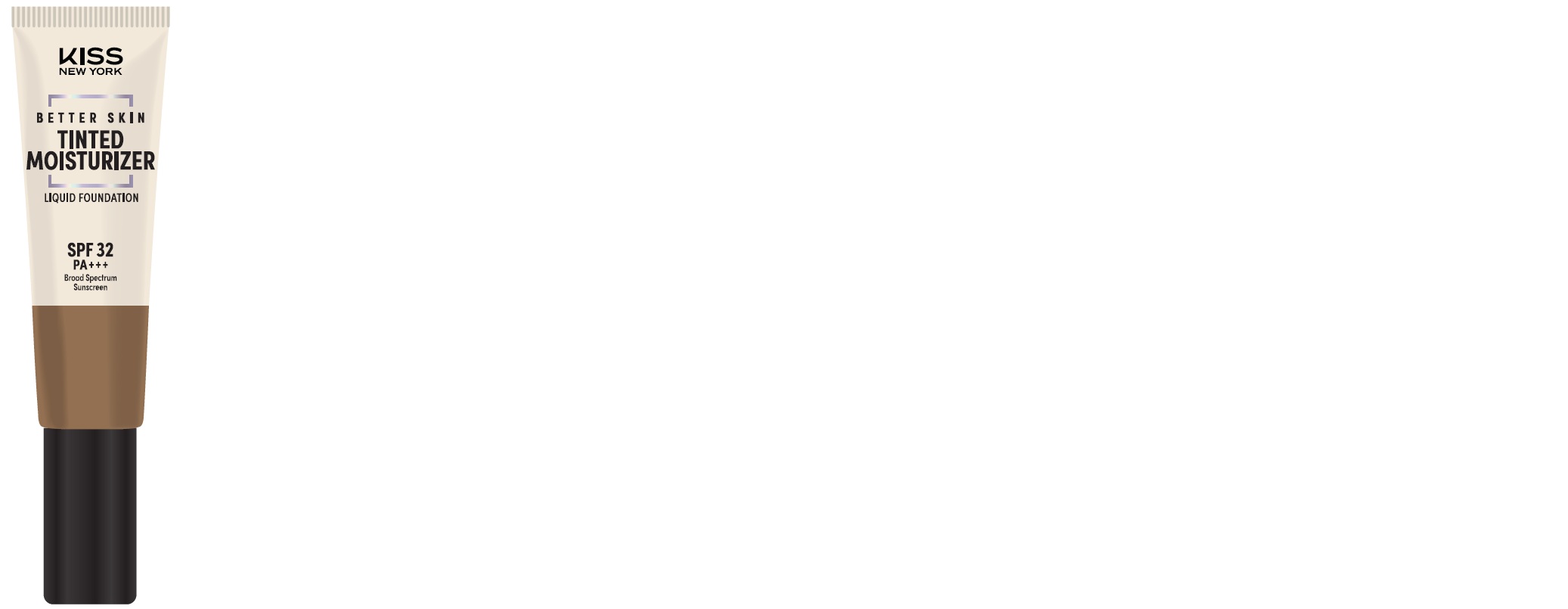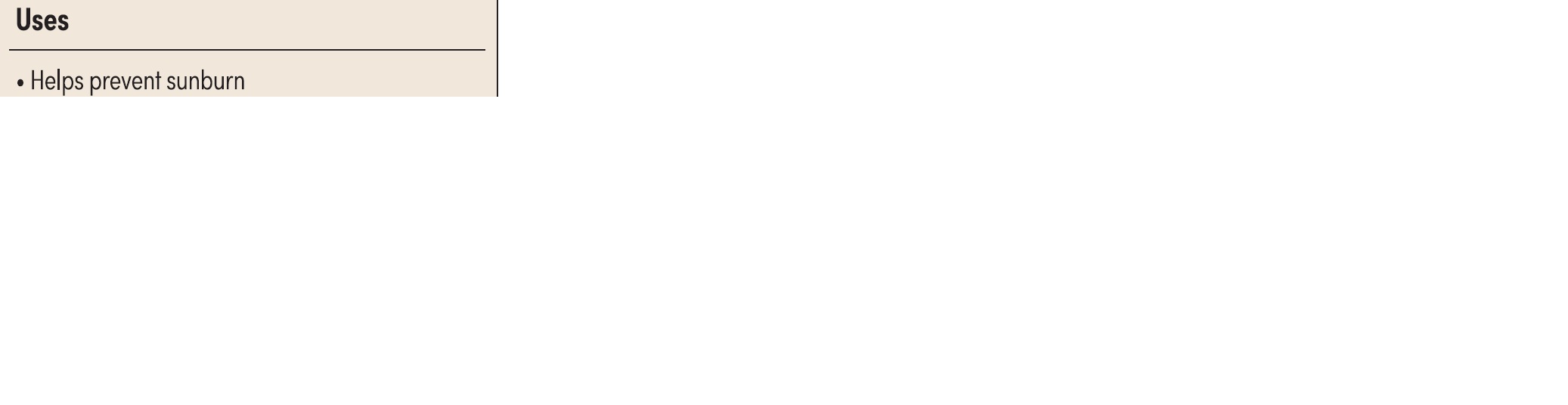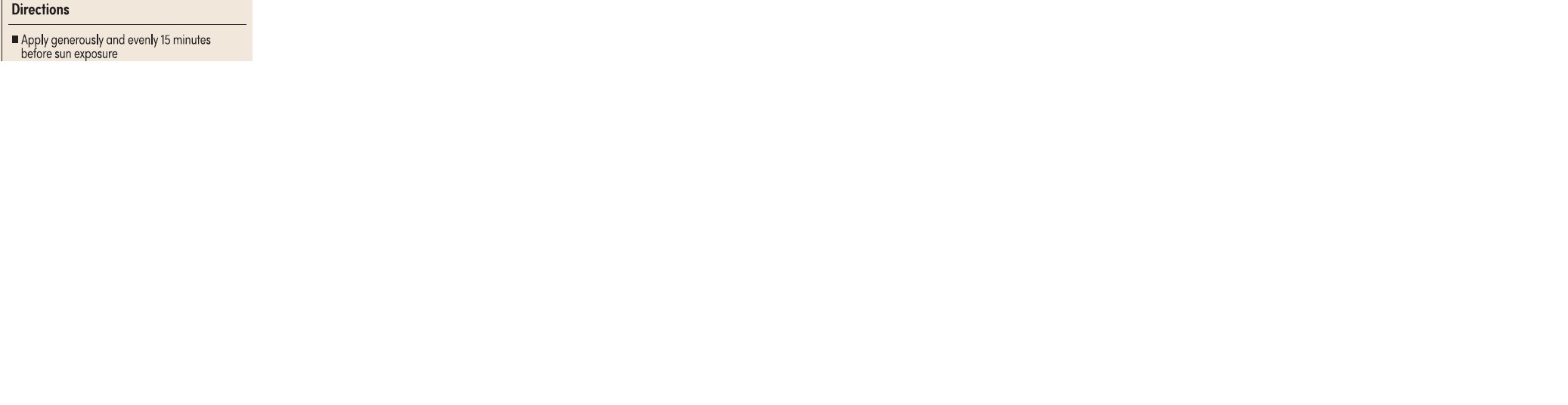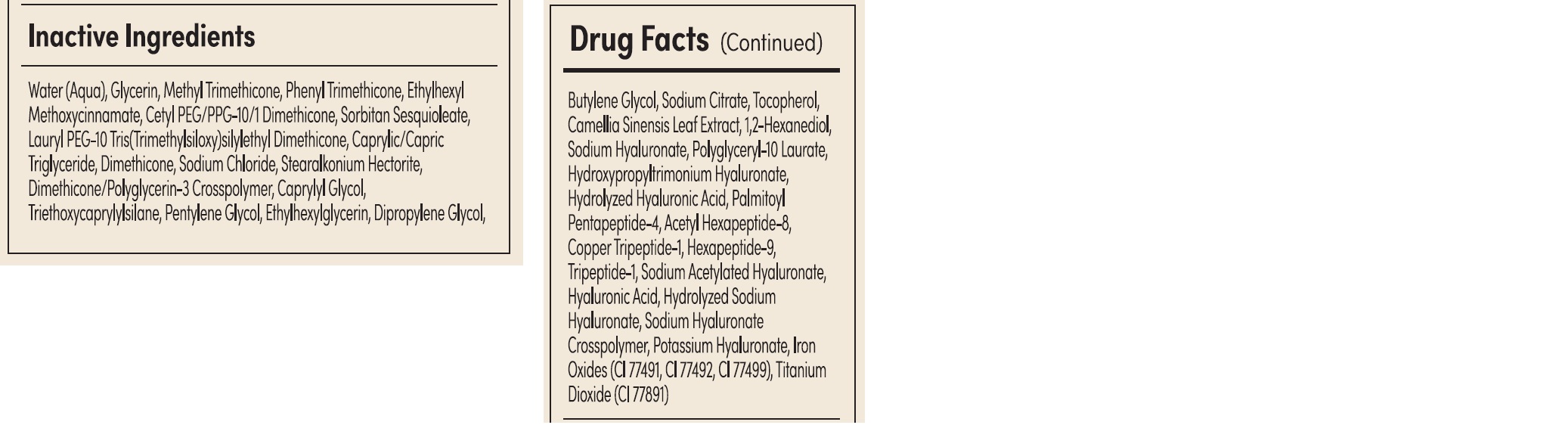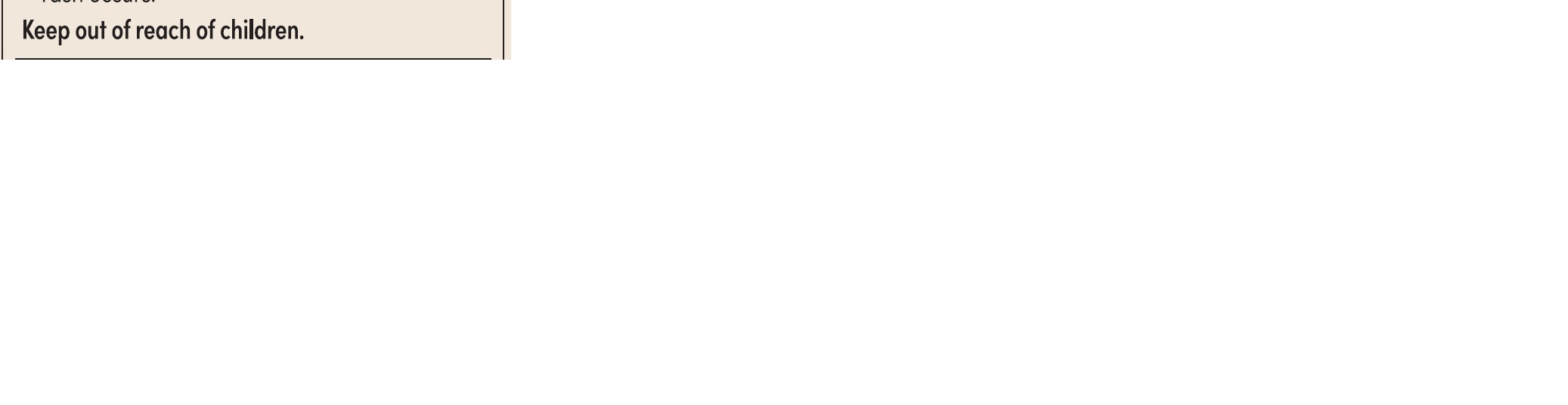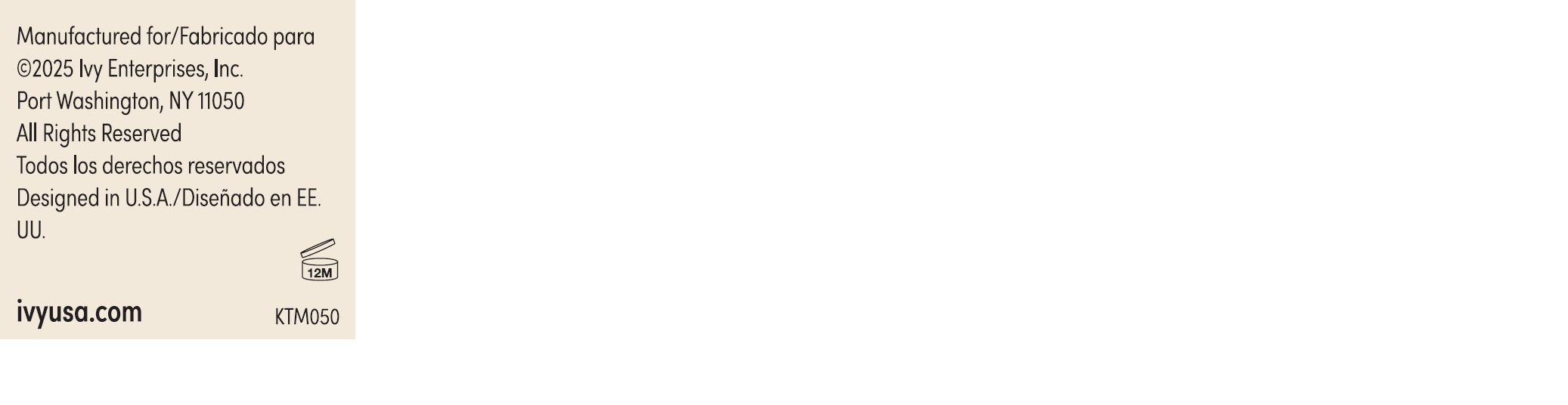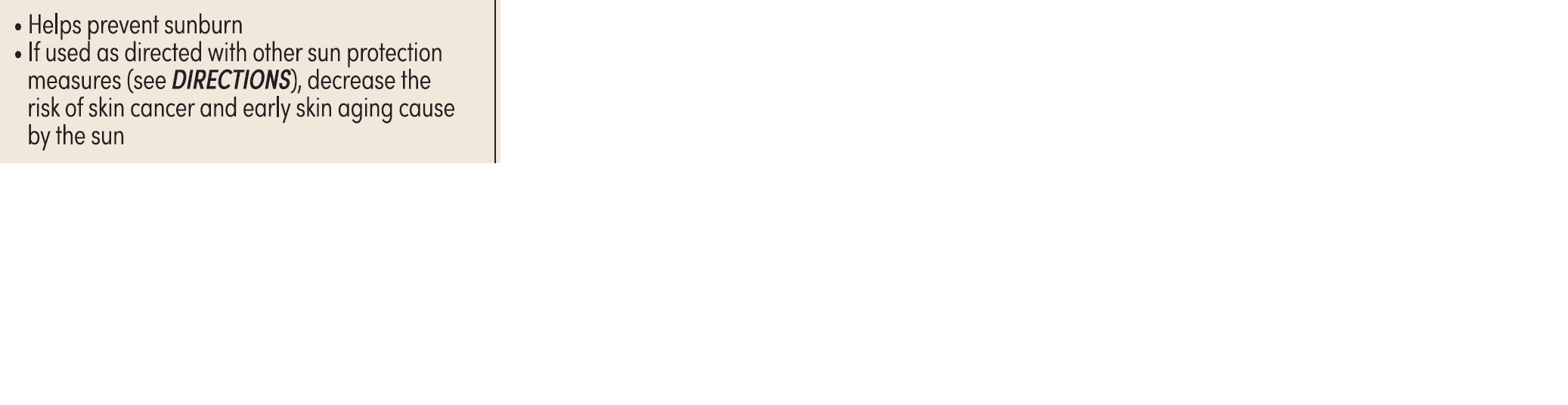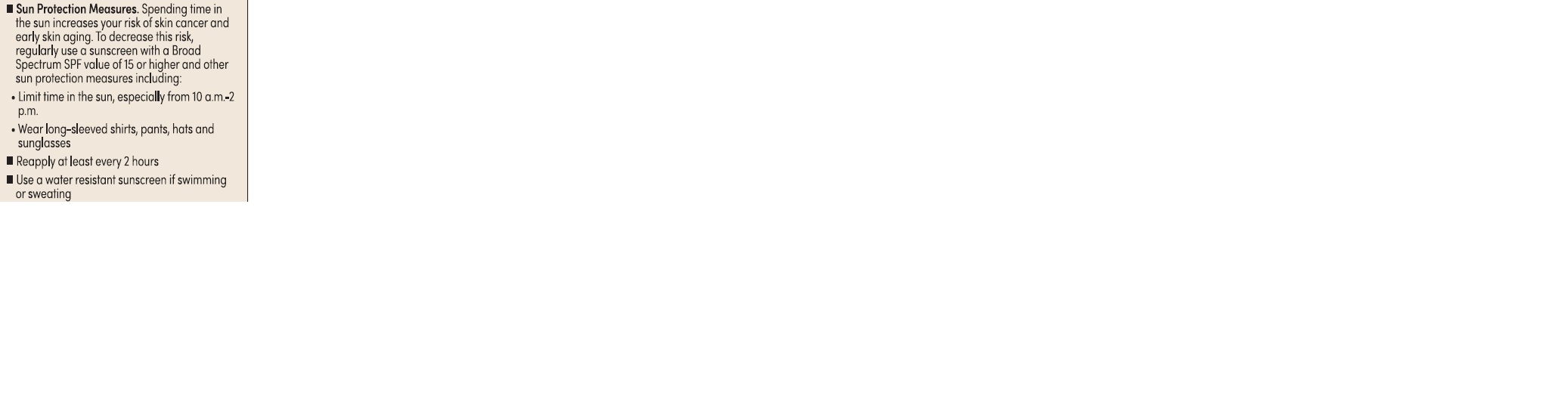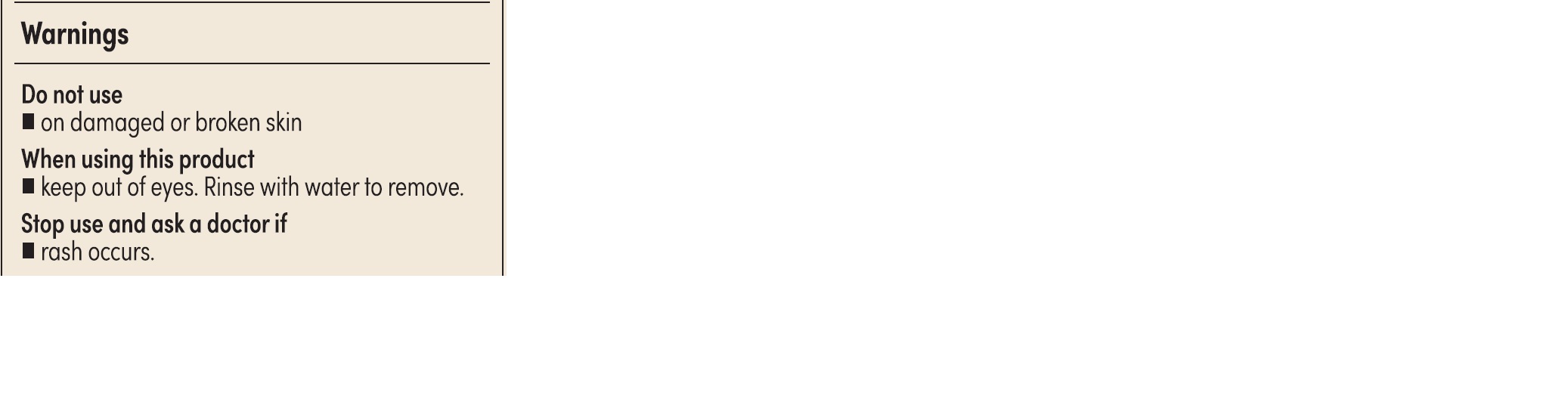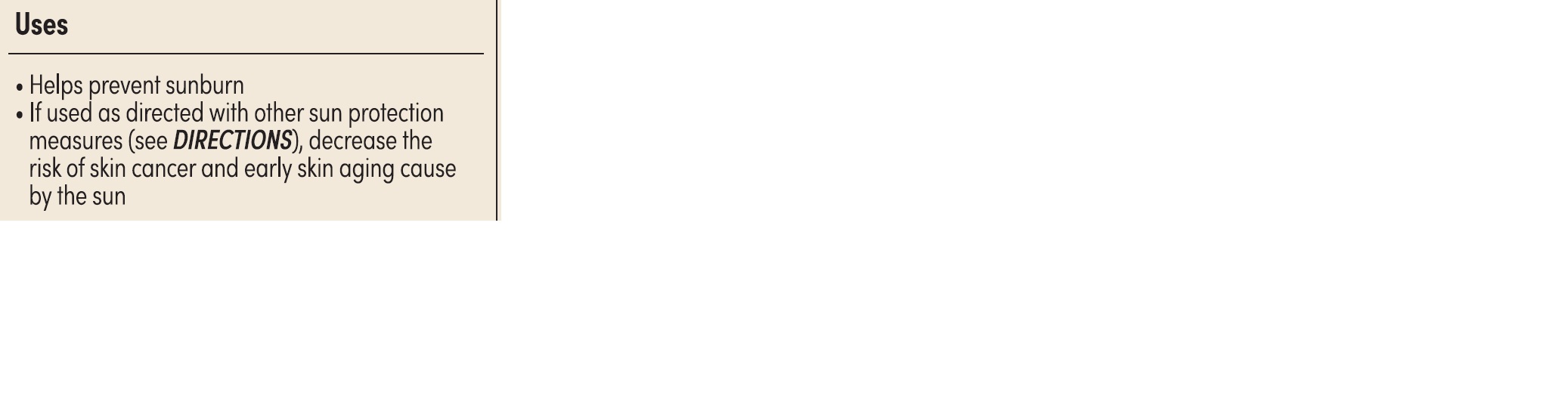 DRUG LABEL: KISS New York Tinted Moisturizer
NDC: 79906-332 | Form: CREAM
Manufacturer: IVY ENTERPRISES, INC.
Category: otc | Type: HUMAN OTC DRUG LABEL
Date: 20250324

ACTIVE INGREDIENTS: ZINC OXIDE 3.5 mg/100 g
INACTIVE INGREDIENTS: DIMETHYLSILANOL HYALURONATE; TITANIUM DIOXIDE; METHYL TRIMETHICONE; DIMETHICONE; PHENYL TRIMETHICONE; PENTYLENE GLYCOL; 1,2-HEXANEDIOL; PALMITOYL PENTAPEPTIDE-4; ACETYL HEXAPEPTIDE-8; TRIPEPTIDE-1; ETHYLHEXYL METHOXYCINNAMATE; STEARALKONIUM HECTORITE; SODIUM CITRATE; TOCOPHEROL; SODIUM HYALURONATE; CAMELLIA SINENSIS LEAF; CI 77499; WATER; DIMETHICONE/POLYGLYCERIN-3 CROSSPOLYMER; DIPROPYLENE GLYCOL; TRIETHOXYCAPRYLYLSILANE; COPPER TRIPEPTIDE-1; BUTYLENE GLYCOL; CETYL PEG/PPG-10/1 DIMETHICONE (HLB 2); CAPRYLIC/CAPRIC TRIGLYCERIDE; GLYCERIN; PEG-10 DIMETHICONE (600 CST); SODIUM CHLORIDE; ETHYLHEXYLGLYCERIN; HYALURONIC ACID; HEXAPEPTIDE-9; SODIUM ACETYLATED HYALURONATE; PEG-9 DIGLYCIDYL ETHER/SODIUM HYALURONATE CROSSPOLYMER; SORBITAN SESQUIOLEATE; CAPRYLYL GLYCOL; POLYGLYCERYL-10 LAURATE; CI 77492; CI 77491

Kiss New York Tinted Moisturizer KTM332 CLASSIC TAN